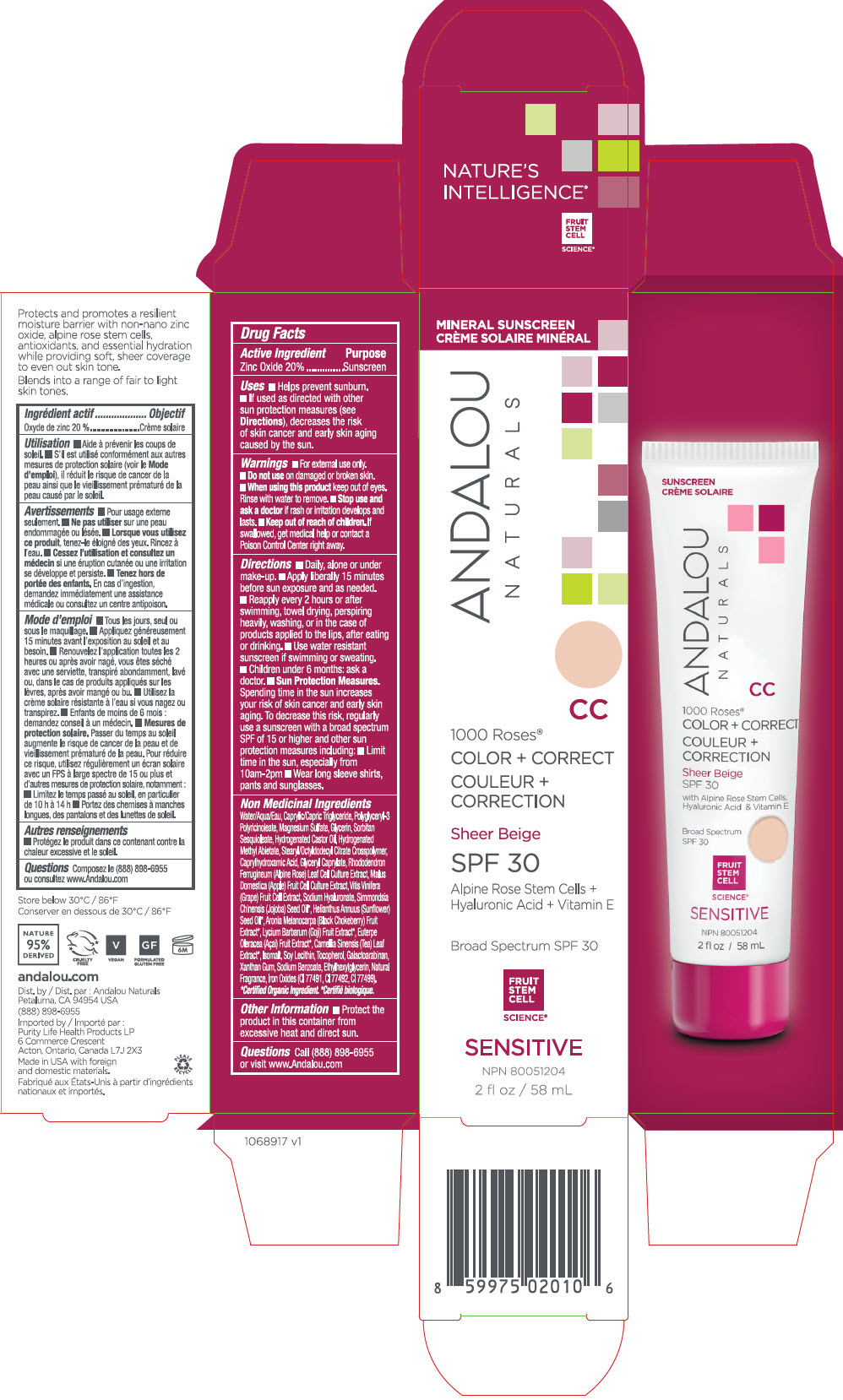 DRUG LABEL: 1000 Roses CC Color plus Correct Sheer Beige SPF 30
NDC: 55560-0110 | Form: LOTION
Manufacturer: Andalou naturals
Category: otc | Type: HUMAN OTC DRUG LABEL
Date: 20250617

ACTIVE INGREDIENTS: ZINC OXIDE 200 mg/1 mL
INACTIVE INGREDIENTS: WATER; MEDIUM-CHAIN TRIGLYCERIDES; POLYGLYCERYL-3 PENTARICINOLEATE; MAGNESIUM SULFATE, UNSPECIFIED FORM; GLYCERIN; SORBITAN SESQUIOLEATE; HYDROGENATED CASTOR OIL; HYDROGENATED METHYL ABIETATE; STEARYL/OCTYLDODECYL CITRATE CROSSPOLYMER; CAPRYLHYDROXAMIC ACID; GLYCERYL MONOCAPRYLATE; RHODODENDRON FERRUGINEUM LEAF; APPLE; VITIS VINIFERA HIGH TANNIN CULTIVAR FRUIT CELL LYSATE; HYALURONATE SODIUM; JOJOBA OIL; SUNFLOWER OIL; ARONIA MELANOCARPA FRUIT JUICE; LYCIUM BARBARUM FRUIT; ACAI; TEA LEAF; ISOMALT; SOYBEAN LECITHIN; TOCOPHEROL; GALACTOARABINAN; XANTHAN GUM; SODIUM BENZOATE; ETHYLHEXYLGLYCERIN; FERRIC OXIDE RED; FERRIC OXIDE YELLOW; FERROSOFERRIC OXIDE

1000 Roses® CC Color + Correct Sheer Beige SPF 30

Drug Facts

Active Ingredient

Zinc Oxide 20%

Purpose

Sunscreen

Uses

- Helps prevent sunburn.

Warnings

- For external use only.

- Do not use on damaged or broken skin.

- When using this product keep out of eyes. Rinse with water to remove.

- Stop use and ask a doctor if rash or irritation develops and lasts.

- Keep out of reach of children. If swallowed, get medical help or contact a Poison Control Center right away.

Directions

- Daily, alone or under make-up.
- Apply liberally 15 minutes before sun exposure and as needed.
- Reapply every 2 hours or after swimming, towel drying, perspiring heavily, washing, or in the case of products applied to the lips, after eating or drinking.
- Use water resistant sunscreen if swimming or sweating.
- Sun Protection Measures. Spending time in the sun increases your risk of skin cancer and early skin aging. To decrease this risk, regularly use a sunscreen with a broad spectrum SPF of 15 or higher and other sun protection measures including: limit time in the sun, especially from 10am-2pm, wear long sleeve shirts, pants and sunglasses.
- Children under 6 months: ask a doctor.

Non Medicinal Ingredients

Water/Aqua/Eau, Caprylic/Capric Triglyceride, Polyglyceryl-3 Polyricinoleate, Magnesium Sulfate, Glycerin, Sorbitan Sesquioleate, Hydrogenated Castor Oil, Hydrogenated Methyl Abietate, Stearyl/Octyldodecyl Citrate Crosspolymer, Caprylhydroxamic Acid, Glyceryl Caprylate, Rhododendron Ferrugineum (Alpine Rose) Leaf Cell Culture Extract, Malus Domestica (Apple) Fruit Cell Culture Extract, Vitis Vinifera (Grape) Fruit Cell Extract, Sodium Hyaluronate, Simmondsia Chinensis (Jojoba) Seed Oil [Certified Organic Ingredient.] , Helianthus Annuus (Sunflower) Seed Oil, Aronia Melanocarpa (Black Chokeberry) Fruit Extract, Lycium Barbarum (Goji) Fruit Extract, Euterpe Oleracea (Açai) Fruit Extract, Camellia Sinensis (Tea) Leaf Extract, Isomalt, Soy Lecithin, Tocopherol, Galactoarabinan, Xanthan Gum, Sodium Benzoate, Ethylhexylglycerin, Natural Fragrance, Iron Oxides (CI 77491, CI 77492, Cl 77499).

Other Information

- Protect the product in this container from excessive heat and direct sun.

Questions

Call (888) 898-6955 or visit www.Andalou.com

Dist. by Andalou Naturals
Novato, CA 94945 USA

PRINCIPAL DISPLAY PANEL - 58 mL Tube Carton

MINERAL SUNSCREEN

ANDALOU
NATURALS

CC

1000 Roses®
COLOR + CORRECT

Sheer Beige

SPF 30

Alpine Rose Stem Cells +
Hyaluronic Acid + Vitamin E

Broad Spectrum SPF 30

FRUIT
STEM
CELL
SCIENCE®

SENSITIVE

NPN 80051204

2 fl oz / 58 mL